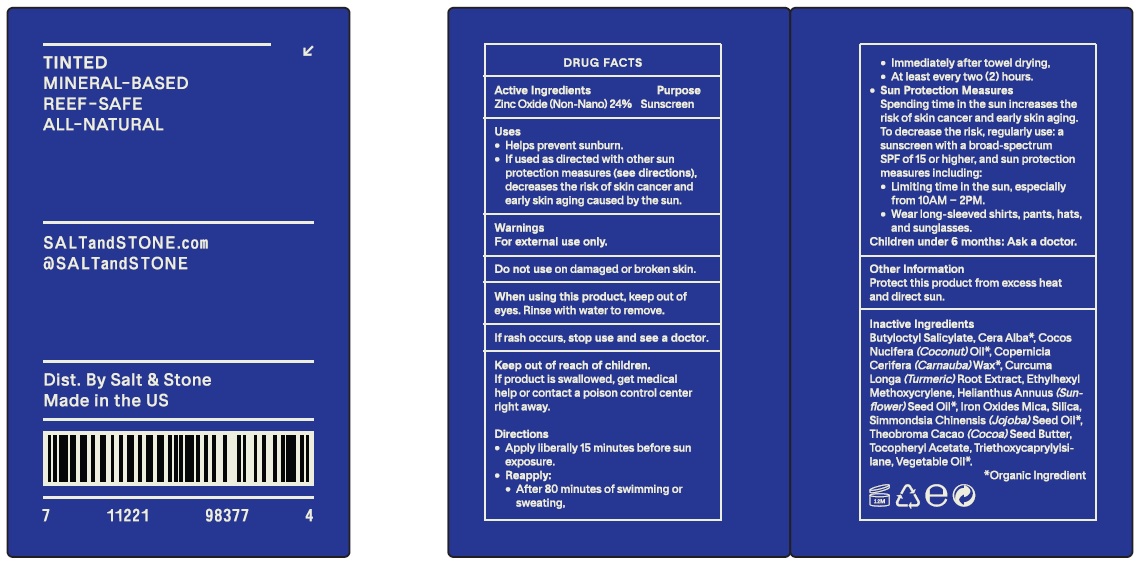 DRUG LABEL: Salt and Stone Outdoor Voices SPF 50
NDC: 71585-143 | Form: STICK
Manufacturer: Salt & Stone, Inc.
Category: otc | Type: HUMAN OTC DRUG LABEL
Date: 20231028

ACTIVE INGREDIENTS: ZINC OXIDE 240 mg/1 g
INACTIVE INGREDIENTS: CORN OIL; WHITE WAX; JOJOBA OIL; BUTYLOCTYL SALICYLATE; COCONUT OIL; CARNAUBA WAX; TURMERIC; ETHYLHEXYL METHOXYCRYLENE; SUNFLOWER OIL; FERRIC OXIDE RED; MICA; COCOA BUTTER; .ALPHA.-TOCOPHEROL ACETATE; TRIETHOXYCAPRYLYLSILANE

Salt & Stone Outdoor Voices SPF 50

Active Ingredients

Zinc Oxide (Non-Nano) 24%

Purpose

Sunscreen

Uses

- Helps prevent sunburn.
- If used as directed with other sun protection measures (see directions), decreases the risk of skin cancer and early skin aging caused by the sun.

Warnings

For external use only.

Do not use

on damaged or broken skin.

When using this product,

keep out of eyes. Rinse with water to remove.

If rash occurs,

Keep out of reach of children.

If product is swallowed, get medical help or contact a poison control center right away.

Directions

- Apply liberally 15 minutes before sun exposure.
- Reapply:
- After 80 minutes of swimming or sweating,
- Immediately after towel drying,
- At least every two (2) hours.
- Sun Protection Measures Spenidng time in the sun increases the risk of skin cancer and early skin aging. To decrease the risk, regularly use: a sunscreen with a broad-spectrum SPF of 15 or higher, and sun protection measures including:
- Limiting time in the sun, especially from 10AM - 2PM.
- Wear long-sleeved shirts, pants, hats, and sunglasses.

Children undre 6 months: Ask a doctor.

Other Information

Protect this product from excess heat and direct sun.

Inactive Ingredients

Butyloctyl Salicylate, Cera Alba*, Cocos Nucifera (Coconut) Oil*, Copernicia Cerifera (Carnauba) Wax*, Curcuma Longa (Turmeric) Root Extract, Ethylhexyl Methoxycrylene, Helianthus Annuus (Sun flower) Seed Oil*, Iron Oxides, Mica, Silica Simmondsia Chinensis (Jojoba) Seed Oil*, Theobroma Cacao (Cocoa) Seed Butter, Tocopheryl Acetate, Triethoxycaprylylsilane, Vegetable Oil*. *Organic Ingredient